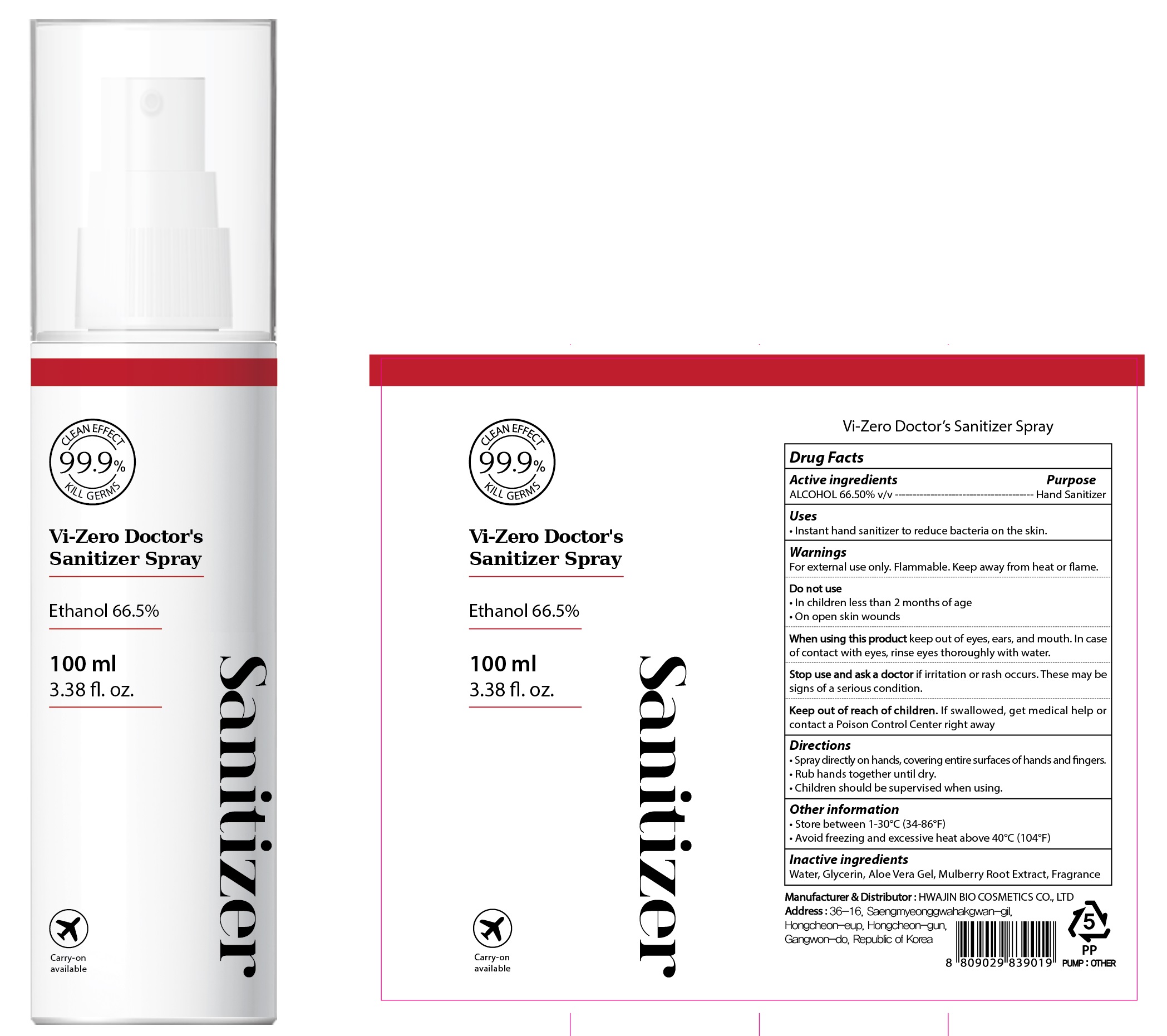 DRUG LABEL: Vi Zero Doctors Sanitizer
NDC: 78394-020 | Form: SPRAY
Manufacturer: HWAJIN BIO COSMETICS CO., LTD.
Category: otc | Type: HUMAN OTC DRUG LABEL
Date: 20200529

ACTIVE INGREDIENTS: ALCOHOL 66.50 mL/100 mL
INACTIVE INGREDIENTS: Water; Glycerin; ALOE VERA LEAF

ACTIVE INGREDIENT

ALCOHOL 66.50% v/v

INACTIVE INGREDIENTS

Water, Glycerin, Aloe Vera Gel, Mulberry Root Extract, Fragrance

PURPOSE

Hand Sanitizer

WARNINGS

For external use only. Flammable. Keep away from heat or flame.
--------------------------------------------------------------------------------------------------------
Do not use
• In children less than 2 months of age
• On open skin wounds
--------------------------------------------------------------------------------------------------------
When using this product keep out of eyes, ears, and mouth. In case of contact with eyes, rinse eyes thoroughly with water.
--------------------------------------------------------------------------------------------------------
Stop use and ask a doctor if irritation or rash occurs. These may be signs of a serious condition.

KEEP OUT OF REACH OF CHILDREN

If swallowed, get medical help or contact a Poison Control Center right away.

Uses

Instant hand sanitizer to reduce bacteria on the skin.

Directions

• Spray directly on hands, covering entire surfaces of hands and fingers.
• Rub hands together until dry.
• Children should be supervised when using.

Other information

• Store between 1-30°C (34-86°F)
• Avoid freezing and excessive heat above 40°C (104°F)